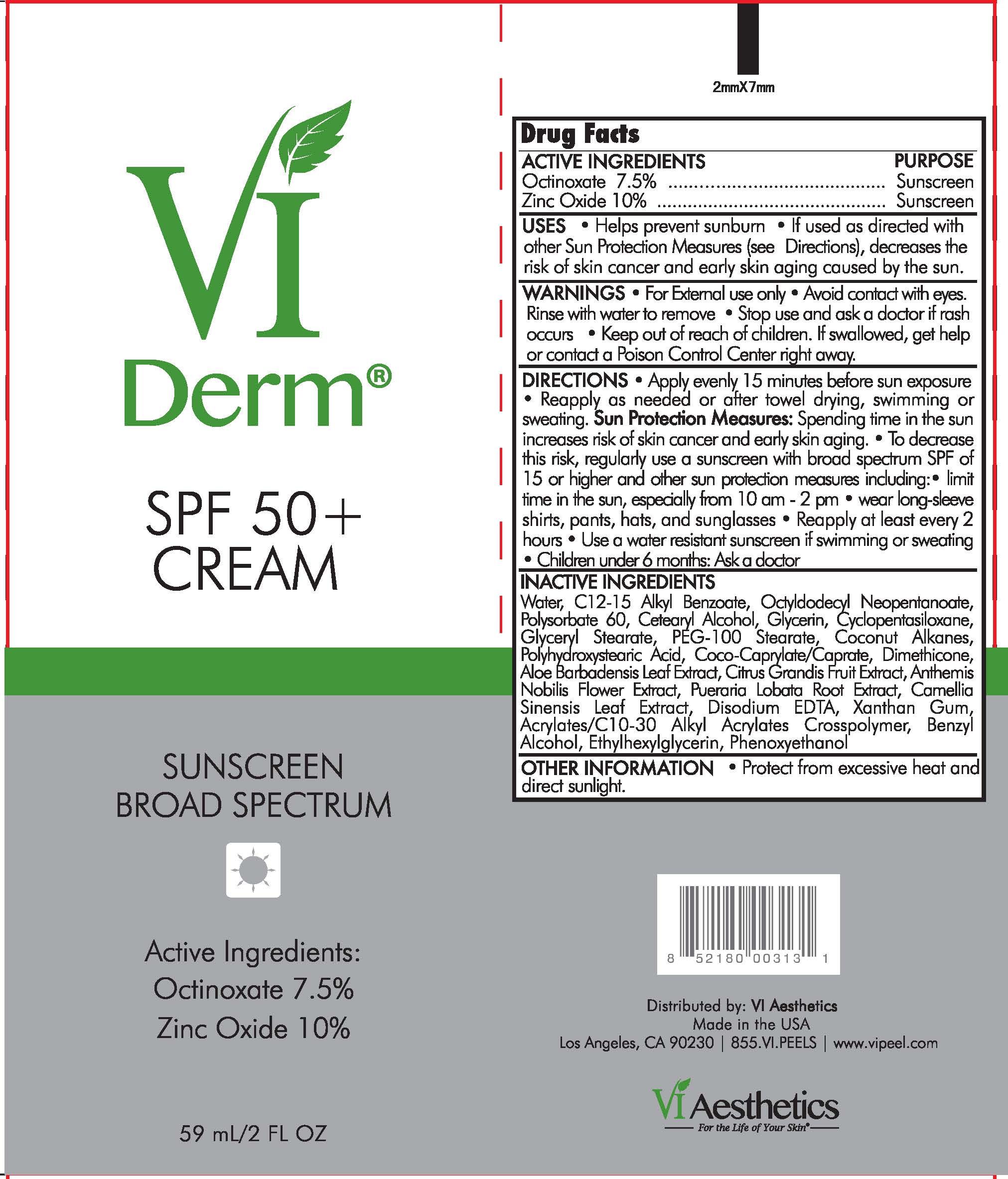 DRUG LABEL: Sunscreen Broad Spectrum SPF 50
NDC: 70484-005 | Form: CREAM
Manufacturer: Vi Medical Products, INC
Category: otc | Type: HUMAN OTC DRUG LABEL
Date: 20250214

ACTIVE INGREDIENTS: ZINC OXIDE 10 g/100 mL; OCTINOXATE 7.5 g/100 mL
INACTIVE INGREDIENTS: ALKYL (C12-15) BENZOATE; WATER; OCTYLDODECYL NEOPENTANOATE; POLYSORBATE 60; CETOSTEARYL ALCOHOL; GLYCERIN; CYCLOMETHICONE 5; GLYCERYL MONOSTEARATE; PEG-100 STEARATE; COCONUT ALKANES; POLYHYDROXYSTEARIC ACID (2300 MW); COCO-CAPRYLATE/CAPRATE; DIMETHICONE; ALOE VERA LEAF; PUMMELO; CHAMAEMELUM NOBILE FLOWER; PUERARIA MONTANA VAR. LOBATA ROOT; GREEN TEA LEAF; EDETATE DISODIUM; XANTHAN GUM; CARBOMER COPOLYMER TYPE A (ALLYL PENTAERYTHRITOL CROSSLINKED); BENZYL ALCOHOL; ETHYLHEXYLGLYCERIN; PHENOXYETHANOL

Sunscreen Broad Spectrum SPF 50 Cream

Active Ingredients Purpose

Octinoxate 7.5% ............. Sunscreen

Zinc Oxide 10% ............... Sunscreen

Uses

- Helps prevent sunburn
- If used as directed with other sun protection measures (see Directions), decreases the risk of skin cancer and early skin aging caused by the sun.

- Keep out of reach of children. If swallowed, get help or contact a Poison Control Center right away.

- Stop use and ask a doctor if rash occurs

Warnings

- For external use only
- When using this product keep out of eyes. Rinse with water to remove

Directions

- Apply evenly 15 minutes before sun exposure
- Reapply at least every 2 hours or after towel drying, swimming or sweating
- Sun protection Measures: Spending time in the sun increases risk of skin cancer and early skin aging. To decrease the risk, regularyly use a sun screen with a Broad Spectrum SPF value of 15 or higher and other sun protection measures including
- Sun protection Measures: Spending time in the sun increases risk of skin cancer and early skin aging. To decrease the risk, regularyly use a sun screen with a Broad Spectrum SPF value of 15 or higher and other sun protection measures including:
- limit time in the sun, especially from 10am-2pm
- wear long-sleeved shirts, pants, hats, and sunglasses
- children under 6 months of age: Askj a doctor

Inactive Ingredients

Water, C12-15, Alkyl Benzoate, Octyldodecly Neopentanoate, Polysorbate 60, Cetearyl Alcohol, Glycerin, Cyclopentasiloxane, Glyceryl Stearate, PEG - 100 Stearate, Coconut Alkanes, Polyhydroxystearic Acid, Coco-Caprylate/Caprate, Dimethicone, Aloe Barbadensis Leaf Extract, Citrus Grandis Fruit Extract, Anthemis Nobilis Flower Extract, Pueraria Lobata Root Extract, Camellia Sinensis Leaf Extract, Disodium EDTA, Xanthan Gum, Acrylates/C10-30 Alkyl Acrylates Crosspolymer, Benzyl Alcohol, Ehtylhexylglycerin, Phenoxyethanol

PACKAGE LABEL

VI Derm

SPF 50+ Cream

Sunscreen Broad Spectrum

59 ml/2 FL OZ